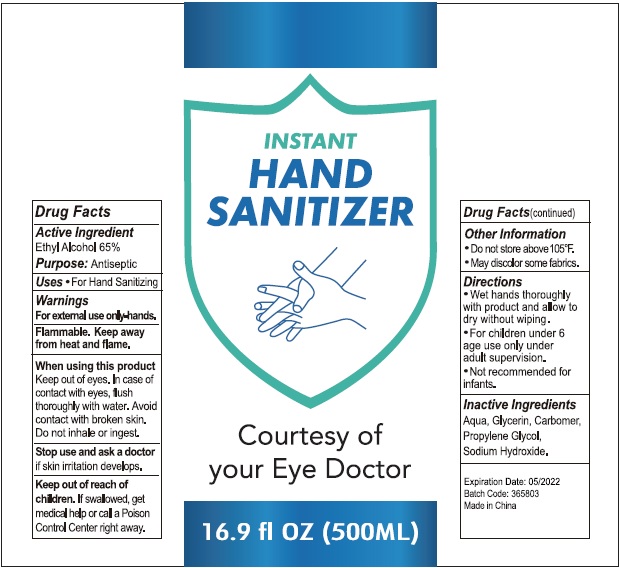 DRUG LABEL: Instant Hand Sanitizer
NDC: 74274-005 | Form: SOLUTION
Manufacturer: Huizhou Bliss Commodity Co., Ltd
Category: otc | Type: HUMAN OTC DRUG LABEL
Date: 20200424

ACTIVE INGREDIENTS: ALCOHOL 65 mL/100 mL
INACTIVE INGREDIENTS: WATER; CARBOMER INTERPOLYMER TYPE A (ALLYL SUCROSE CROSSLINKED); GLYCERIN; PROPYLENE GLYCOL; SODIUM HYDROXIDE

Active ingredient

Ethyl Alcohol 65%

Purpose

Antiseptic

Use

For hand Sanitizing

KEEP OUT OF REACH OF CHILDREN

if swallowed, get medical help or contact a Poison Control Center right away.

warnings:

Flamable, keep away from heat and flames

For external use only

When using this product

Keep out of eye, In case of contact with eyes, flush thoroughly with water. Avoid contact with broken skin. Do not inhale or ingest.

Stop and ask a doctor

if skin irritation develops.

Directions

- Wet hands thoroughly with product and allow to dry without wiping.
- For children under 6 age use only under adult supervision.
- Not recommended for infants.

Other information

- Do not store above 105℉。
- May discolor some fabrics.

Inactive ingredients

Aqua, glycerin, carbomer, propyene glycol, sodium hydroxide.